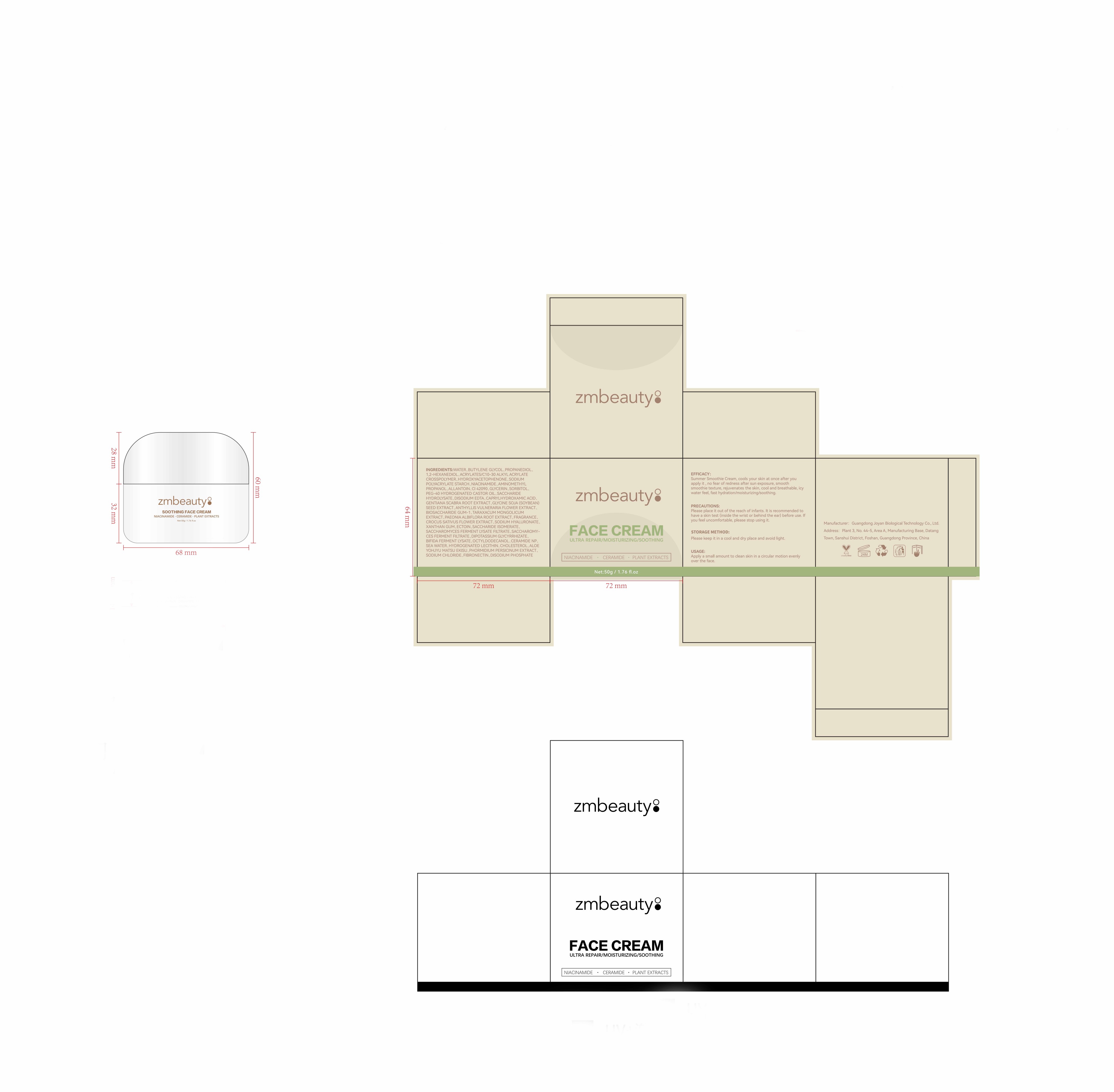 DRUG LABEL: xiufumianshuang
NDC: 84716-111 | Form: EMULSION
Manufacturer: Shenzhen Boyang E-commerce Co.
Category: otc | Type: HUMAN OTC DRUG LABEL
Date: 20240924

ACTIVE INGREDIENTS: HYDROXYACETOPHENONE 17.5 mg/50 g; NIACINAMIDE 10 mg/50 g; BUTYLENE GLYCOL 150 mg/50 g; PROPANEDIOL 115 mg/50 g
INACTIVE INGREDIENTS: WATER 45.9 g/50 g; GLYCERIN 5 mg/50 g

Active ingredients

BUTYLENE GLYCOL 3%
PROPANEDIOL 2.3%
HYDROXYACETOPHENONE 0.35%
NIACINAMIDE 0.2%

PURPOSE

ULTRA REPAIR/MOISTURIZING/SOOTHING/anti-wrinkle/whiten/Spot Removal and Lightening/Facial Lifting & Firming/antioxidant

uses

Apply a small amount to clean skin in a circular motion evenly over the face.

Warnings

Please place it out of the reach of infants. lt is recommended to have a skin test (inside the wrist or behind the ear) before use. lf you feel uncomfortable, please stop using it.

Stop use and ask a doctor if

lt is recommended to have a skin test (inside the wrist or behind the ear) before use. lf you feel uncomfortable, please stop using it.

Do not use

on damaged or broken skin

When using this product

keep out of eyes. Rinse with water to remove

INACTIVE INGREDIENT SECTION

WATER 91.8%
GLYCERIN 0.1%

Uses and STORAGE METHOD

Apply a small amount to clean skin in a circular motion evenly over the face. please keep it in a cool and dry place and avoid light